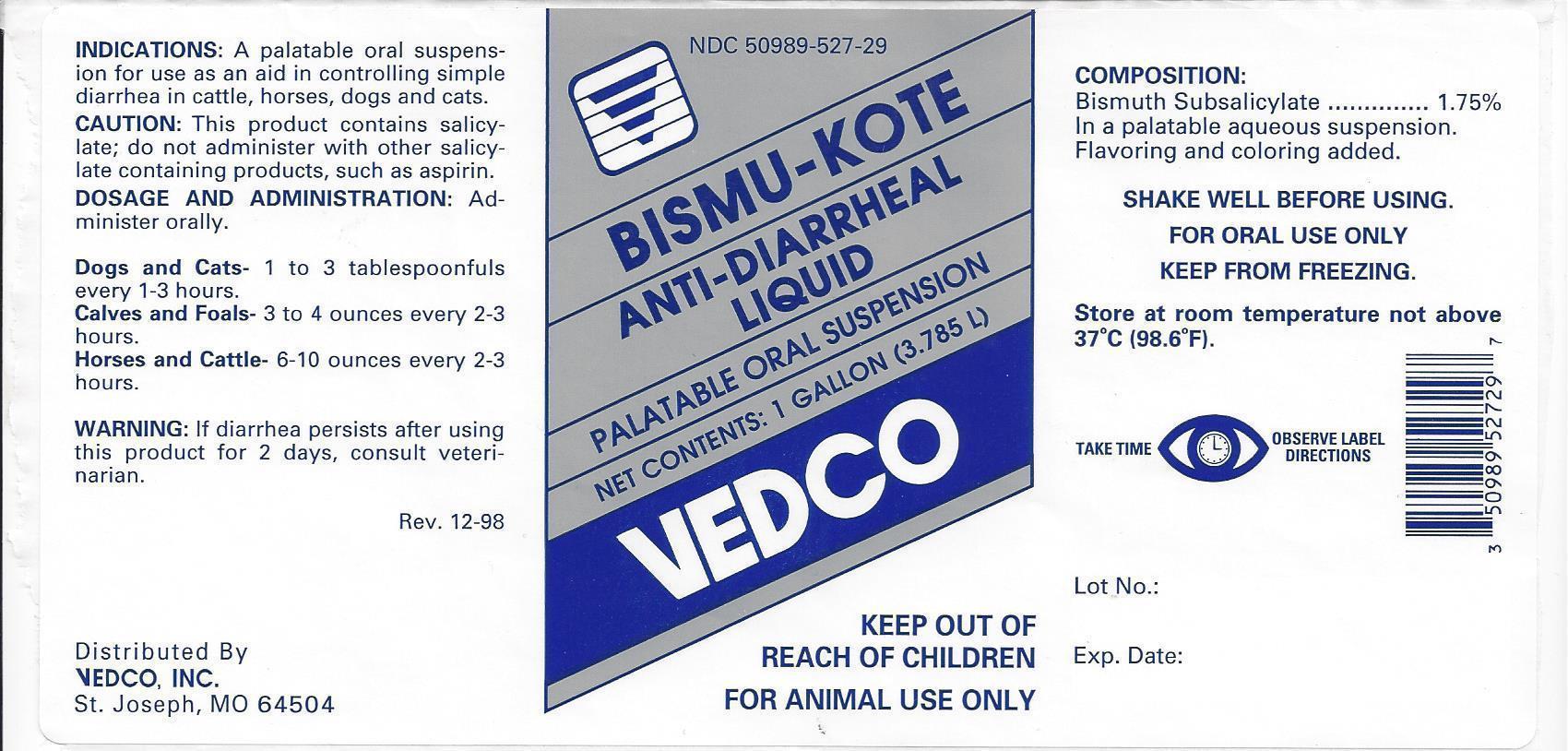 DRUG LABEL: Bismuth
NDC: 50989-527 | Form: SUSPENSION
Manufacturer: VEDCO
Category: animal | Type: OTC ANIMAL DRUG LABEL
Date: 20130917

ACTIVE INGREDIENTS: BISMUTH SUBSALICYLATE 18 mg/1 mL
INACTIVE INGREDIENTS: GUAR GUM; POTASSIUM SORBATE; SACCHARIN SODIUM; METHYL SALICYLATE; WATER; D&C RED NO. 33; SILICON DIOXIDE

VEDCO BISMU-KOTE

NDC 50989-527-29 BISMU-KOTE ANTI-DIARRHEAL LIQUID PALATABLE ORAL SUSPENSION

NET CONTENTS: 1 GALLON (3.785 L)

VEDCO

KEEP OUT OF REACH OF CHILDREN

FOR ANIMAL USE ONLY

INDICATIONS:

A palatable oral suspension for use as an aid in controlling simple diarrhea in cattle, horses, dogs and cats.

CAUTION:

This product contains salicylate; do not administer with other salicylate-containing products, such as aspirin.

DOSAGE AND ADMINISTRATION:

Administer orally

Dogs and Cats- 1 to 3 tablespoonfuls every 1-3 hours

Calves and Foals- 3 to 4 ounces every 2-3 hours

Horses and Cattle- 6 to 10 ounces every 2-3 hours

WARNING:

If diarrhea persists after using this product for 2 days, contact a veterinarian.

Rev 12-98

Distributed By

VEDCO, INC.

St. Joseph, MO 64504

COMPOSITION:

Bismuth Subsalicylate............1.75%

In a palatable aqueous suspension.

Flavoring and coloring added.

SHAKE WELL BEFORE USING.

FOR ORAL USE ONLY

KEEP FROM FREEZING.

STORAGE AND HANDLING

Store at room temperature above 37ºC (98.6ºF).

TAKE TIME OBSERVE LABEL DIRECTIONS

Lot No.:

Exp. Date: